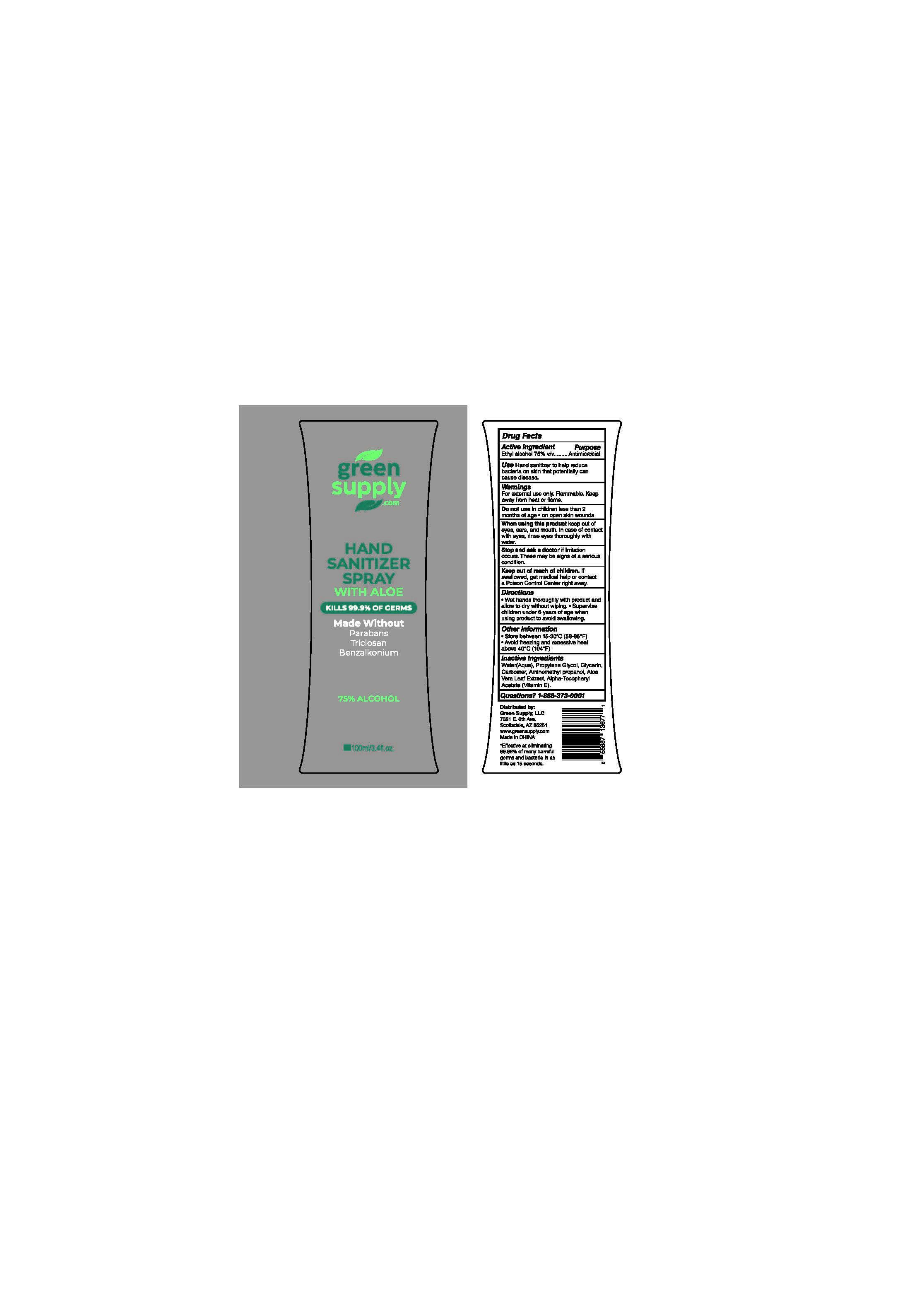 DRUG LABEL: Hand Sanitizer
NDC: 74796-002 | Form: SPRAY
Manufacturer: GreenSupply.com LLC
Category: otc | Type: HUMAN OTC DRUG LABEL
Date: 20201012

ACTIVE INGREDIENTS: ALCOHOL 75 mL/100 mL
INACTIVE INGREDIENTS: ALPHA-TOCOPHEROL ACETATE; PROPYLENE GLYCOL; GLYCERIN; AMINOMETHYLPROPANOL; WATER; ALOE VERA LEAF; CARBOMER HOMOPOLYMER, UNSPECIFIED TYPE

Green Supply Updated Formula

Active Ingredient(s)

Ethyl Alcohol 75% v/v. Purpose: Antimicrobial

Purpose

Antimicrobial, Hand Sanitizer

Use

Hand Sanitizer to help reduce bacteria that potentially can cause disease.

Warnings

For external use only. Flammable. Keep away from heat or flame

Do not use

- in children less than 2 months of age
- on open skin wounds

When using this product keep out of eyes, ears, and mouth. In case of contact with eyes, rinse eyes thoroughly with water.
Stop use and ask a doctor if irritation occurs. These may be signs of a serious condition.
Keep out of reach of children. If swallowed, get medical help or contact a Poison Control Center right away.

Stop use and ask a doctor if irritation or rash occurs. These may be signs of a serious condition.

Keep out of reach of children. If swallowed, get medical help or contact a Poison Control Center right away.

Directions

- Wet hands thoroughly with product and allow to dry without wiping.
- Supervise children under 6 years of age when using this product to avoid swallowing.

Other information

- Store between 15-30C (59-86F)
- Avoid freezing and excessive heat above 40C (104F)

Inactive ingredients

water (aqua), glycerin, propylene glycol, carbomer, aminomethylpropanol, aloe vera leaf, alpha-tocopheryl acetate (vitamin e)

Package Label - Principal Display Panel

100 mL NDC: 74796-002-01